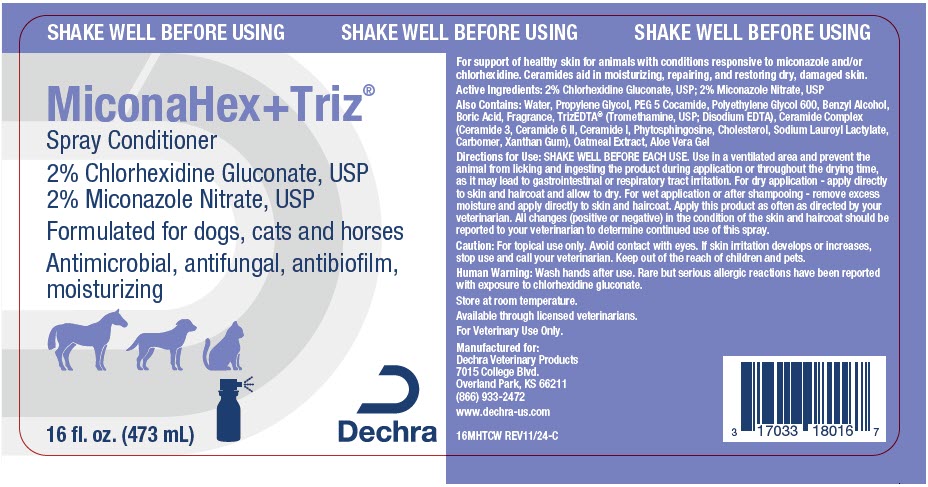 DRUG LABEL: MiconaHex Plus Triz Conditioner
NDC: 17033-180 | Form: SPRAY, SUSPENSION
Manufacturer: Dechra Veterinary Products
Category: animal | Type: OTC ANIMAL DRUG LABEL
Date: 20241212

ACTIVE INGREDIENTS: CHLORHEXIDINE GLUCONATE 20 mg/1 mL; MICONAZOLE NITRATE 20 mg/1 mL

MiconaHex + Triz® Spray Conditioner

VETERINARY INDICATIONS

For support of healthy skin for animals with conditions responsive to miconazole and/or chlorhexidine. Ceramides aid in moisturizing, repairing, and restoring dry, damaged skin.

DESCRIPTION

Active Ingredients: 2% Chlorhexidine Gluconate, USP; 2% Miconazole Nitrate, USP

Also Contains: Water, PEG- 8, Polysorbate 80, Cyclodextrin, Benzyl Alcohol, Lactose Monohydrate, Polysorbate 20, Fragrance, Ceramide Complex (Ceramide 3, Ceramide 6 II, Ceramide I, Phytosphingosine, Cholesterol, Sodium Lauroyl Lactylate, Carbomer, Xanthan Gum), Citric Acid, TrizEDTA® (Tromethamine, USP; Disodium EDTA)

DOSAGE AND ADMINISTRATION

Directions for Use: SHAKE WELL BEFORE EACH USE. For dry application - apply directly to skin and haircoat and allow to dry. For wet application or after shampooing - remove excess moisture and apply directly to skin and haircoat. Apply this product as often as directed by your veterinarian. All changes (positive or negative) in the condition of the skin and haircoat should be reported to your veterinarian to determine continued use of this spray.

PRECAUTIONS

Caution: For topical use only. Avoid contact with eyes. If skin irritation develops or increases, stop use and call your veterinarian. Keep out of the reach of children and pets.

WARNINGS

Human Warning: Wash hands after use. Rare but serious allergic reactions have been reported with exposure to chlorhexidine gluconate.

STORAGE AND HANDLING

Store at room temperature.

Available through licensed veterinarians.

For Veterinary Use Only.

Manufactured for: Dechra Veterinary Products
7015 College Blvd., Overland Park, KS 66211
866.933.2472
www.dechra-us.com

16MHTCW REV10/22

PRINCIPAL DISPLAY PANEL - 473 mL Bottle Label

SHAKE WELL BEFORE USING

MiconaHex+Triz®

Spray Conditioner
2% Chlorhexidine Gluconate, USP
2% Miconazole Nitrate, USP
Formulated for dogs, cats and horses
Antimicrobial, antifungal, antibiofilm,
moisturizing

16 fl. oz. (473 mL)

Dechra